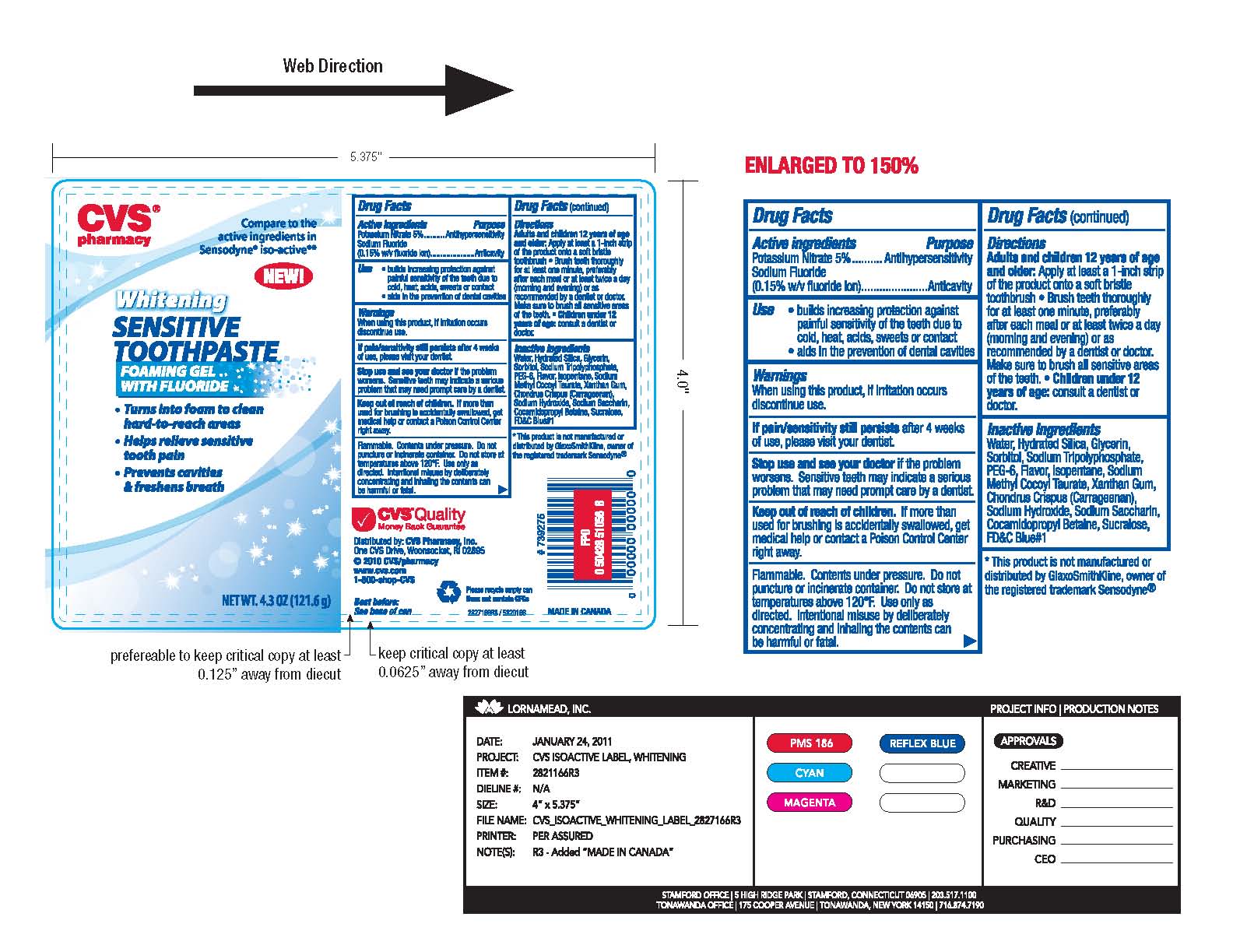 DRUG LABEL: Sensitive Tooth Paste
NDC: 59779-816 | Form: GEL
Manufacturer: CVS Pharmacy
Category: otc | Type: HUMAN OTC DRUG LABEL
Date: 20111214

ACTIVE INGREDIENTS: POTASSIUM NITRATE 5.0 g/100 g; SODIUM FLUORIDE 0.15 g/100 g
INACTIVE INGREDIENTS: SORBITOL 24.0 g/100 g; WATER 22.0697 g/100 g; SACCHARIN SODIUM 0.2 g/100 g; SUCRALOSE 0.01 g/100 g; POLYETHYLENE GLYCOL 300 3.0 g/100 g; FD&C BLUE NO. 1 0.0003 g/100 g; GLYCERIN 19.0 g/100 g; XANTHAN GUM 0.7 g/100 g; CHONDRUS CRISPUS 0.7 g/100 g; HYDRATED SILICA 19.0 g/100 g; SODIUM METHYL COCOYL TAURATE 1.0 g/100 g; COCAMIDOPROPYL BETAINE 0.4 g/100 g; ISOPENTANE; SODIUM HYDROXIDE 0.48 g/100 g; SODIUM TRIPOLYPHOSPHATE

Drug Facts

Active ingredients

POTASSIUM NITRATE 5% .........................................HYPERSENSITIVITY
SODIUM FLUORIDE (0.15% W/V) FLUORIDE ION.........ANTICAVITY

Use

- builds increasing protection against

painful sensitivity of the teeth due to
cold, heat, acids, sweats or contact

- aids in the prevention of dental cavities

Uses

When using this product if irritation occurs
discontinue use
If pain/sensitivity still persists after 4 weeks
of use, please visit your dentist

Keep out of reach of children. If more than

used for brushing is accidentally swallowed, get

medical help or contact a poison control center

right away

Directions

Adults and children 12 years of age
and older: Apply at least a 1- inch strip
of the product onto a soft bristle
toothbrush * Brush teeth thoroughly
for at least one minute, preferably
after each meal or at least twice a day
(morning and evening) or as
recommended by a dentist or doctor.
Make sure to brush all sensitive areas
of the teeth.Children under 12
years of age: consult a dentist or doctor.

Inactive ingredients

Water, Hydrated Silica, Glycerin, Sorbitol, Sodium Tripolyphosphate,
PEG-6, Flavor, Isopentane, Xanthan Gum, Chondrus Crispus (Carrageenan),
Sodium Hydroxide, Sodium Methyl Cocoyl Taurate, Cocomidopropyl Betaine,
Sodium Saccharin, Sucralose, FD C Blue 1

Warnings

Flammable. Contents under pressure.Do not
puncture or incinerate container. Do not store at
temperatures above 120 F. Use only as
directed. Intentional misuse by deliberately
concentrating and inhaling the contents can
be harmful or fatal.